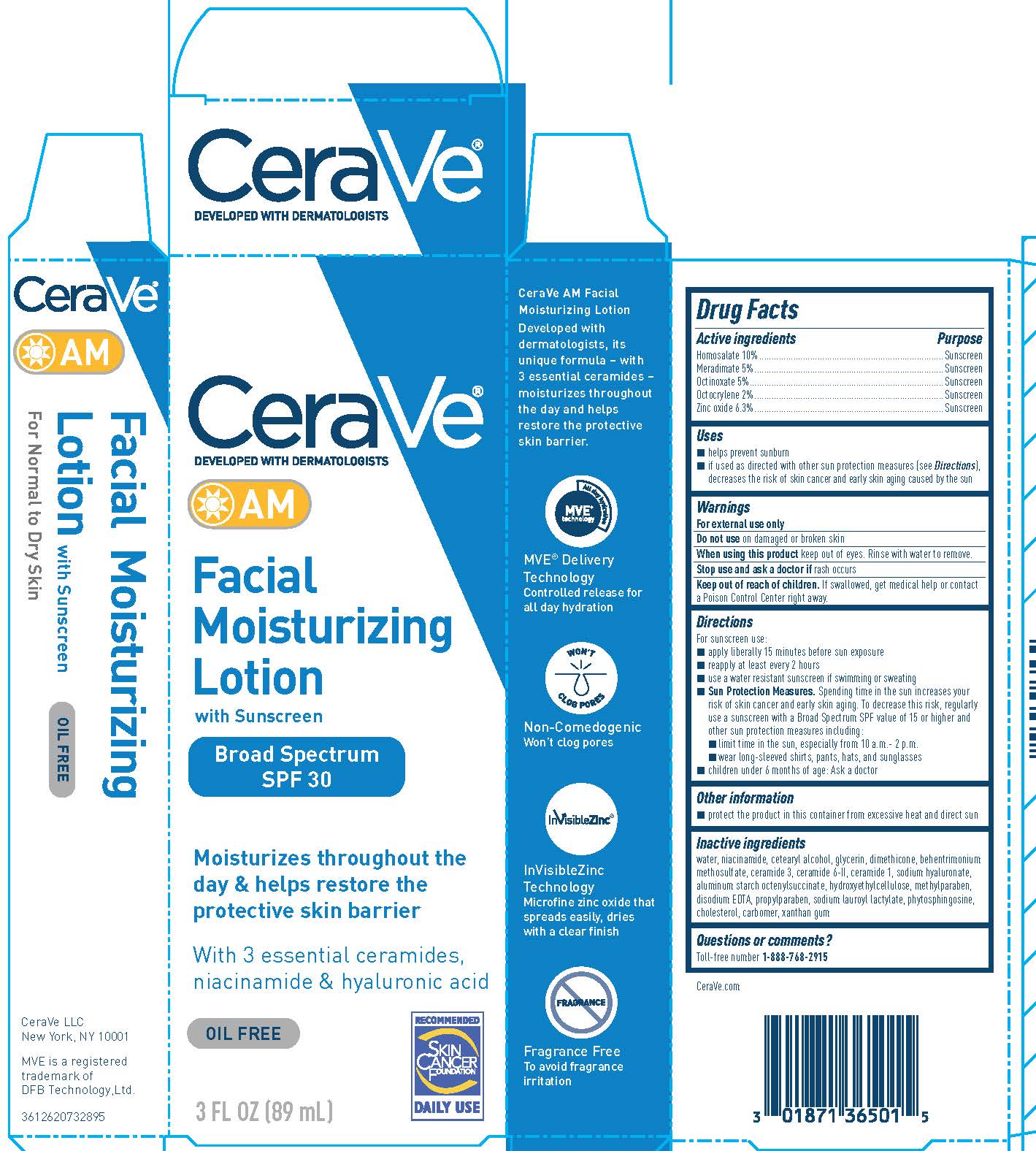 DRUG LABEL: CeraVe AM Facial Moisturizing Broad Spectrum SPF 30 Sunscreen
NDC: 49967-015 | Form: LOTION
Manufacturer: L'Oreal USA Products, Inc.
Category: otc | Type: HUMAN OTC DRUG LABEL
Date: 20231231

ACTIVE INGREDIENTS: Homosalate 100 mg/1 mL; MERADIMATE 50 mg/1 mL; Octinoxate 50 mg/1 mL; Octocrylene 20 mg/1 mL; Zinc oxide 63 mg/1 mL
INACTIVE INGREDIENTS: WATER; NIACINAMIDE; CETOSTEARYL ALCOHOL; GLYCERIN; DIMETHICONE; BEHENTRIMONIUM METHOSULFATE; CERAMIDE 3; CERAMIDE 6 II; CERAMIDE 1; HYALURONIC ACID; SODIUM HYDROXIDE; ALUMINUM STARCH OCTENYLSUCCINATE; HYDROXYETHYL CELLULOSE (4000 MPA.S AT 1%); METHYLPARABEN; EDETATE DISODIUM; PROPYLPARABEN; SODIUM LAUROYL LACTYLATE; PHYTOSPHINGOSINE; CHOLESTEROL; CARBOMER HOMOPOLYMER TYPE A (ALLYL PENTAERYTHRITOL CROSSLINKED); XANTHAN GUM

Drug Facts

Active ingredients

Homosalate 10%

Meradimate 5%

Octinoxate 5%

Octocrylene 2%

Zinc oxide 6.3%

Purpose

Sunscreen

Uses

• helps prevent sunburn
• if used as directed with other sun protection measures (see Directions), decreases the risk of skin cancer and early skin aging caused by the sun

Warnings

For external use only

Do not use

on damaged or broken skin

When using this product

keep out of eyes. Rinse with water to remove.

Stop use and ask a doctor if

rash occurs

Keep out of reach of children.

If swallowed, get medical help or contact a Poison Control Center right away.

Directions

For sunscreen use:
● apply liberally 15 minutes before sun exposure
● reapply at least every 2 hours
● use a water resistant sunscreen if swimming or sweating
● Sun Protection Measures. Spending time in the sun increases your risk of skin cancer and early skin aging. To decrease this risk, regularly use a sunscreen with a Broad Spectrum SPF value of 15 or higher and other sun protection measures including:
● limit time in the sun, especially from 10 a.m. – 2 p.m.
● wear long-sleeved shirts, pants, hats, and sunglasses
● children under 6 months of age: Ask a doctor

Inactive ingredients

water, niacinamide, cetearyl alcohol, glycerin, dimethicone, behentrimonium methosulfate, ceramide 3, ceramide 6-II, ceramide 1, hyaluronic acid, sodium hydroxide, aluminum starch octenylsuccinate, hydroxyethylcellulose, methylparaben, disodium EDTA, propylparaben, sodium lauroyl lactylate, phytosphingosine, cholesterol, carbomer, xanthan gum

Other information

protect the product in this container from excessive heat and direct sun

Questions or comments?

Toll-free number 1-888-768-2915

www.CeraVe.com